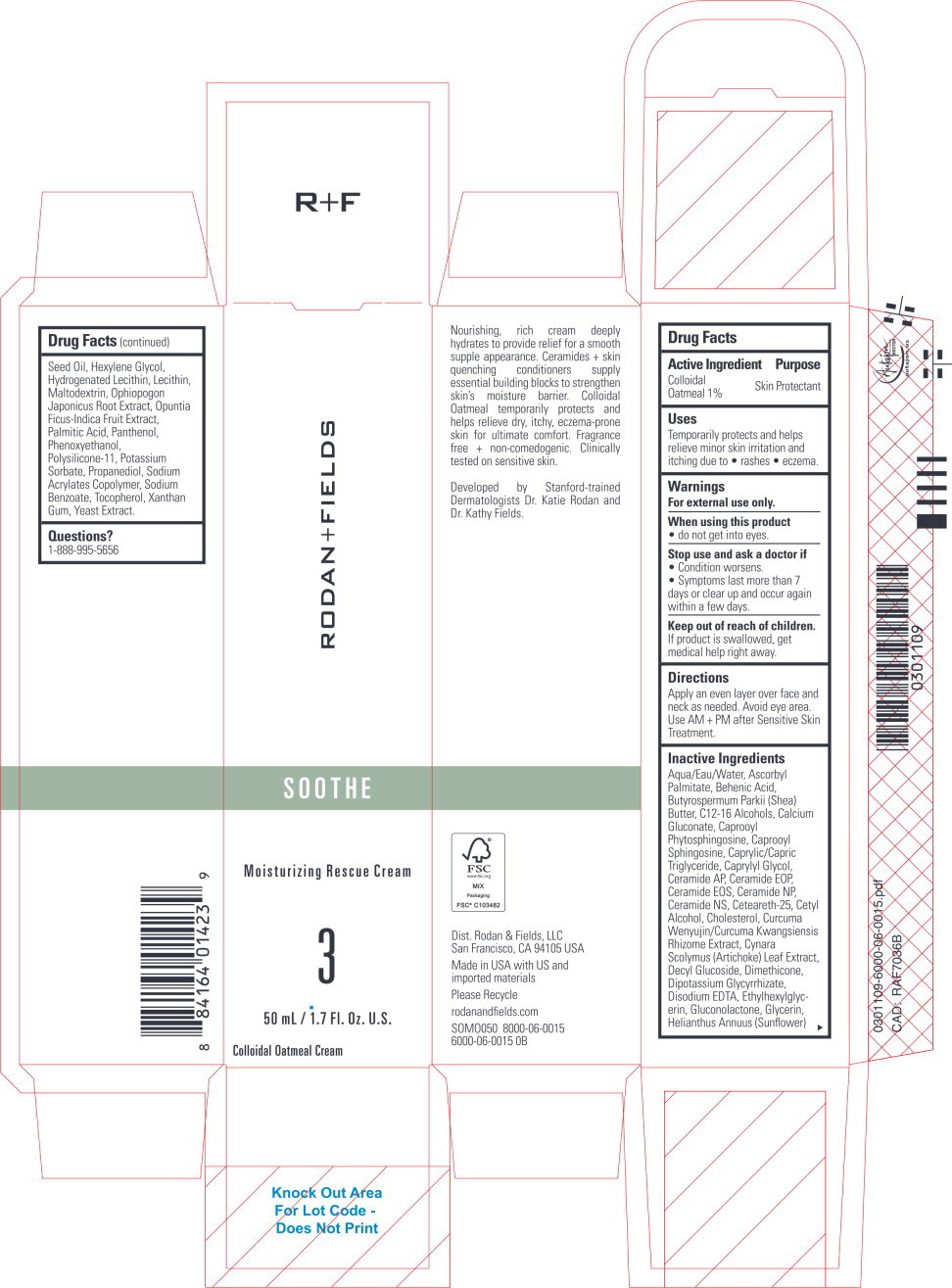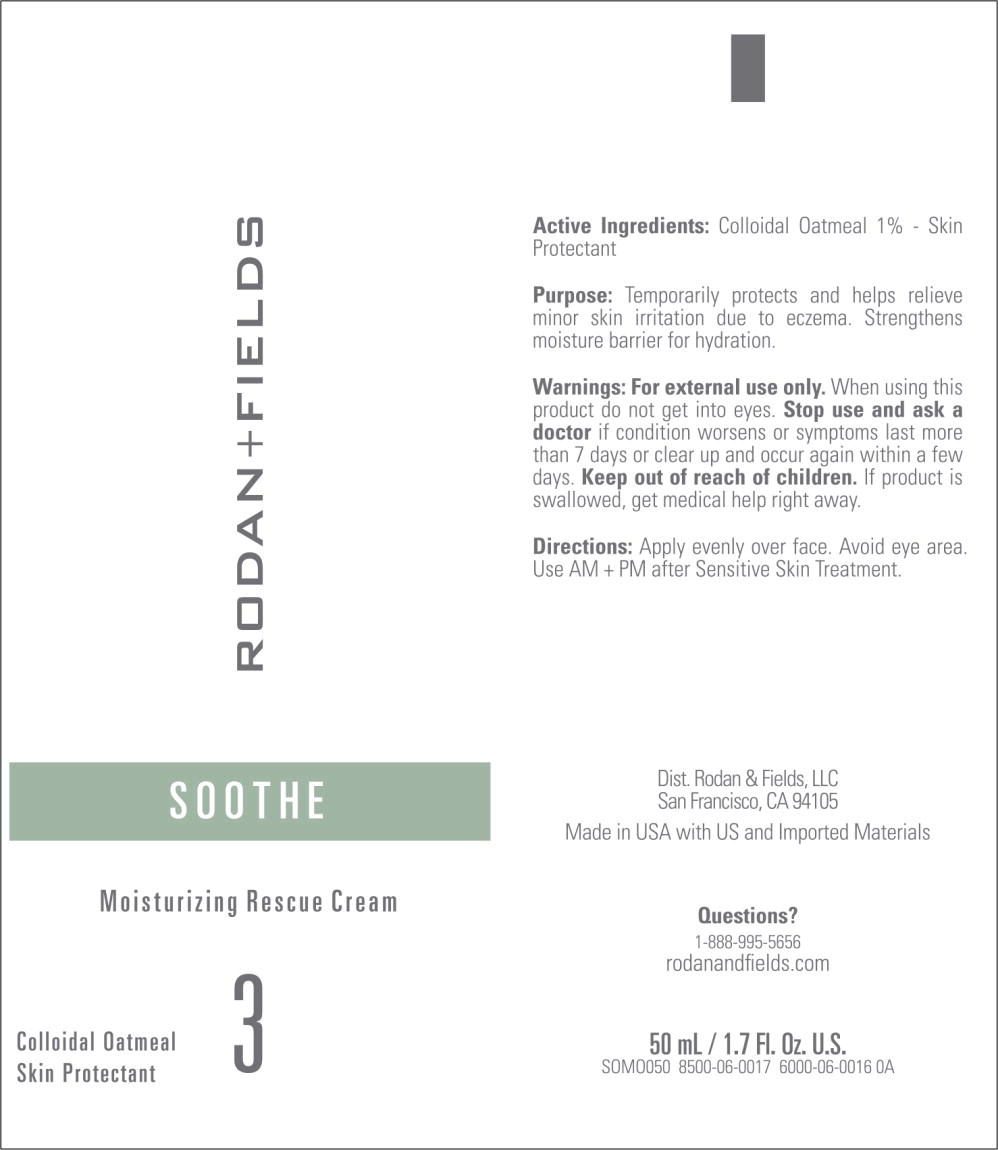 DRUG LABEL: SOOTHE Moisturizing Rescue Cream
NDC: 14222-2430 | Form: CREAM
Manufacturer: Rodan & Fields
Category: otc | Type: HUMAN OTC DRUG LABEL
Date: 20231204

ACTIVE INGREDIENTS: OATMEAL 0.01 g/1 mL
INACTIVE INGREDIENTS: ASCORBYL PALMITATE; BEHENIC ACID; SHEA BUTTER; C12-16 ALCOHOLS; CALCIUM GLUCONATE; N-HEXANOYLSPHINGOSINE; MEDIUM-CHAIN TRIGLYCERIDES; CAPRYLYL GLYCOL; CERAMIDE AP; CERAMIDE 1; CERAMIDE EOS; CERAMIDE NP; CERAMIDE NG; CETEARETH-25; CETYL ALCOHOL; CHOLESTEROL; CURCUMA KWANGSIENSIS ROOT; CYNARA SCOLYMUS LEAF; DECYL GLUCOSIDE; DIMETHICONE; GLYCYRRHIZINATE DIPOTASSIUM; EDETATE DISODIUM ANHYDROUS; ETHYLHEXYLGLYCERIN; GLUCONOLACTONE; GLYCERIN; SUNFLOWER OIL; HEXYLENE GLYCOL; HYDROGENATED SOYBEAN LECITHIN; LECITHIN, SOYBEAN; MALTODEXTRIN; OPHIOPOGON JAPONICUS ROOT; PRICKLY PEAR FRUIT; PALMITIC ACID; PANTHENOL; PHENOXYETHANOL; DIMETHICONE/VINYL DIMETHICONE CROSSPOLYMER (SOFT PARTICLE); POTASSIUM SORBATE; PROPANEDIOL; SODIUM BENZOATE; TOCOPHEROL; WATER; XANTHAN GUM; YEAST, UNSPECIFIED

Drug Facts

Active Ingredient

Colloidal

Oatmeal 1 %

Purpose

Skin Protectant

Uses

Temporarily protects and helps relieve minor skin irritation and itching due to • rashes • eczema.

Warnings

For external use only.

When using this product

- do not get into eyes.

Stop use and ask a doctor if

- Condition worsens.
- Symptoms last more than 7 days or clear up and occur again within a few days.

Keep out of reach of children.

If product is swallowed, get medical help right away.

Directions

Apply an even layer over face and neck as needed. Avoid eye area. Use AM + PM after Sensitive Skin Treatment.

Inactive Ingredients

Aqua/Eau/Water, Ascorbyl Palmitate, Behenic Acid, Butyrospermum Parkii (Shea) Butter, C12-16 Alcohols, Calcium Gluconate, Caprooyl Phytosphingosine, Caprooyl Sphingosine, Caprylic/Capric Triglyceride, Caprylyl Glycol, Ceramide AP, Ceramide EOP, Ceramide EOS, Ceramide NP, Ceramide NS, Ceteareth-25, Cetyl Alcohol, Cholesterol, Curcuma Wenyujin/Curcuma Kwangsiensis Rhizome Extract, Cynara Scolymus (Artichoke) Leaf Extract, Decyl Glucoside, Dimethicone, Dipotassium Glycyrrhizate, Disodium EDTA, Ethylhexylglycerin, Gluconolactone, Glycerin, Helianthus Annuus (Sunflower) Seed Oil, Hexylene Glycol, Hydrogenated Lecithin, Lecithin, Maltodextrin, Ophiopogon Japonicus Root Extract, Opuntia Ficus-lndica Fruit Extract, Palmitic Acid, Panthenol, Phenoxyethanol, Polysilicone-11, Potassium Sorbate, Propanediol, Sodium Acrylates Copolymer, Sodium Benzoate, Tocopherol, Xanthan Gum, Yeast Extract.

Questions?

1-888-995-5656

Principal Display Panel - 50 mL Carton Label

RODAN+FIELDS

SOOTHE

Moisturizing Rescue Cream

3

50 mL/ 1.7 Fl. Oz. U.S.

Colloidal Oatmeal Cream

Principal Display Panel - 50 mL Tube Label

RODAN+FIELDS

SOOTHE

Moisturizing Rescue Cream

3

Colloidal Oatmeal
Skin Protectant